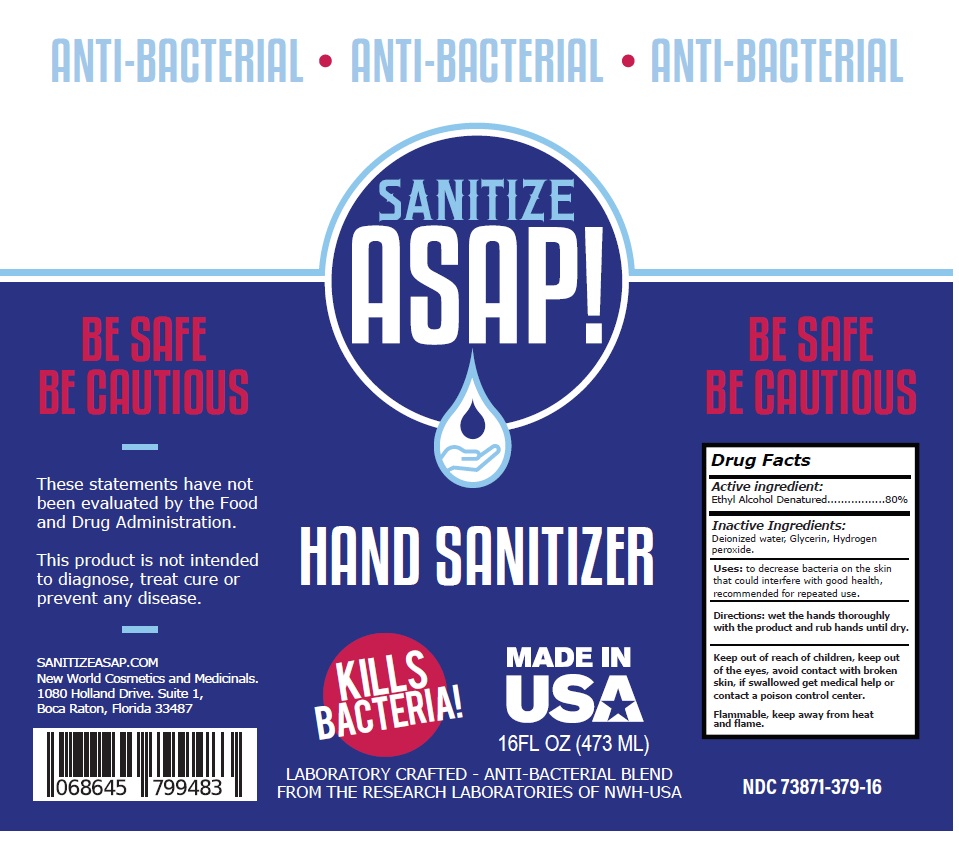 DRUG LABEL: SANITIZE ASAP HAND SANITIZER
NDC: 73871-379 | Form: LIQUID
Manufacturer: New World Holdings, Inc.
Category: otc | Type: HUMAN OTC DRUG LABEL
Date: 20200518

ACTIVE INGREDIENTS: ALCOHOL 0.8 mL/1 mL
INACTIVE INGREDIENTS: WATER; GLYCERIN; HYDROGEN PEROXIDE

SANITIZE ASAP HAND SANITIZER

Active ingredient:

Ethyl Alcohol Denatured.................80%

Purpose:

Antiseptic

Inactive Ingredients:

Deionized water, Glycerin, Hydrogen peroxide.

INDICATIONS AND USAGE

Uses: to decrease bacteria on the skin that could interfere with good health, recommended for repeated use.

DOSAGE AND ADMINISTRATION

Directions: wet the hands thoroughly with the product and rub hands until dry.

WARNINGS

Keep out of reach of children, keep out of the eyes, avoid contact with broken skin, if swallowed get medical help or contact a poison control center.

Flammable, keep away from heat and flame.

ANTI-BACTERIAL

KILLS BACTERIA!

MADE IN USA

LABORATORY CRAFTED - ANTI-BACTERIAL BLEND

FROM THE RESEARCH LABORATORIES OF NWH-USA

BE SAFE

BE CAUTIOUS

These statements have not been evaluated by the Food and Drug Administration.

This product is not intended to diagnose, treat cure or prevent any disease.

SANITIZEASAP.COM

New World Cosmetics and Medicinals.
1080 Holland Drive. Suite 1,
Boca Raton, Florida 33487